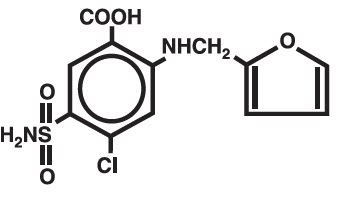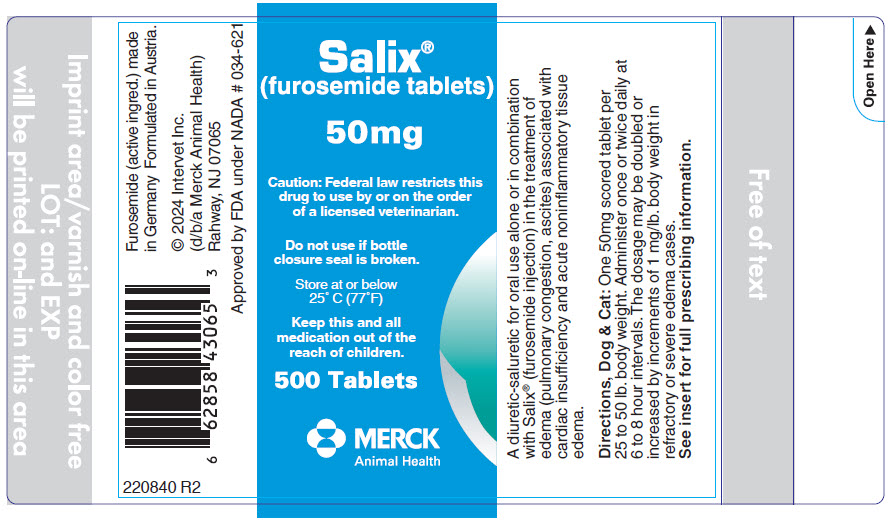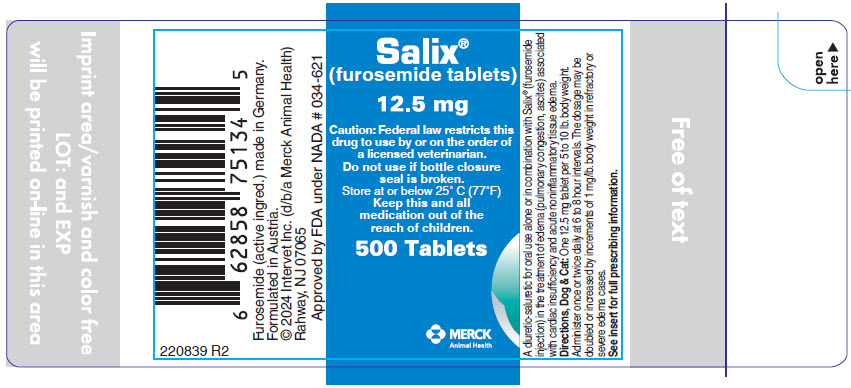 DRUG LABEL: Salix
NDC: 57926-464 | Form: TABLET
Manufacturer: Merck Sharp & Dohme Corp.
Category: animal | Type: PRESCRIPTION ANIMAL DRUG LABEL
Date: 20251030

ACTIVE INGREDIENTS: FUROSEMIDE 50 mg/1 1

Salix®
(furosemide tablets)

FOR USE IN ANIMALS ONLY

VETERINARY INDICATIONS

A diuretic-saluretic for prompt relief of edema.

Caution: Federal law restricts this drug to use by or on the order of a licensed veterinarian.

See package labeling for storage conditions.

DESCRIPTION

Salix® (furosemide tablets) is a chemically distinct diuretic and saluretic pharmacodynamically characterized by the following:

1) A high degree of efficacy, low-inherent toxicity and a high therapeutic index.

2) A rapid onset of action and of comparatively short duration.

3) A pharmacological action in the functional area of the nephron, i.e., proximal and distal tubules and the ascending limb of the loop of Henle.

4) A dose-response relationship and a ratio of minimum to maximum effective dose range greater than tenfold.

5) It may be administered orally or parenterally.

It is readily absorbed from the intestinal tract and well tolerated.

The intravenous route produces the most rapid diuretic response.

The CAS Registry Number is 54-31-9.

Salix®, a diuretic, is an anthranilic acid derivative with the following structural formula:

Generic name: Furosemide (except in United Kingdom-furosemide).

Chemical name: 4-chloro-N-furfuryl-5-sulfamoylanthranilic acid.

CLINICAL PHARMACOLOGY

ACTIONS

The therapeutic efficacy of Salix® is from the activity of the intact and unaltered molecule throughout the nephron, inhibiting the reabsorption of sodium not only in the proximal and distal tubule but also in the ascending limb of the loop of Henle. The prompt onset of action is a result of the drug's rapid absorption and a poor lipid solubility.

The low lipid solubility and a rapid renal excretion minimize the possibility of its accumulation in tissues and organs or crystalluria. Salix® has no inhibitory effect on carbonic anhydrase or aldosterone activity in the distal tubule. The drug possesses diuretic activity either in presence of acidosis or alkalosis.

INDICATIONS

Dogs and Cats

Salix® is an effective diuretic possessing a wide therapeutic range. Pharmacologically it promotes the rapid removal of abnormally retained extracellular fluids. The rationale for the efficacious use of diuretic therapy is determined by the clinical pathology producing the edema. Salix® is indicated for the treatment of edema (pulmonary congestion, ascites) associated with cardiac insufficiency and acute noninflammatory tissue edema.

The continued use of heart stimulants, such as digitalis or its glycosides is indicated in cases of edema involving cardiac insufficiency.

CONTRAINDICATIONS – PRECAUTIONS

PRECAUTIONS

Salix® is a highly effective diuretic-saluretic which if given in excessive amounts may result in dehydration and electrolyte imbalance.

Therefore, the dosage and schedule may have to be adjusted to the patient's needs. The animal should be observed for early signs of electrolyte imbalance, and corrective measures administered. Early signs of electrolyte imbalance are: increased thirst, lethargy, drowsiness or restlessness, fatigue, oliguria, gastro-intestinal disturbances and tachycardia. Special attention should be given to potassium levels. Salix® may lower serum calcium levels and cause tetany in rare cases of animals having an existing hypocalcemic tendency.

Although diabetes mellitus is a rarely reported disease in animals, active or latent diabetes mellitus may on rare occasions be exacerbated by Salix®.

While it has not been reported in animals the use of high doses of salicylates, as in rheumatic diseases, in conjunction with Salix® may result in salicylate toxicity because of competition for renal excretory sites.

Transient loss of auditory capacity has been experimentally produced in cats following intravenous injection of excessive doses of Salix® at a very rapid rate.

Electrolyte balance should be monitored prior to surgery in patients receiving Salix®.

Imbalances must be corrected by administration of suitable fluid therapy.

Salix® is contraindicated in anuria. Therapy should be discontinued in cases of progressive renal disease if increasing azotemia and oliguria occur during the treatment. Sudden alterations of fluid and electrolyte imbalance in an animal with cirrhosis may precipitate hepatic coma, therefore observation during period of therapy is necessary.

In hepatic coma and in states of electrolyte depletion, therapy should not be instituted until the basic condition is improved or corrected. Potassium supplementation may be necessary in cases routinely treated with potassium-depleting steroids.

WARNINGS

Salix® is a highly effective diuretic and if given in excessive amounts as with any diuretic may lead to excessive diuresis which could result in electrolyte imbalance, dehydration and reduction of plasma volume enhancing the risk of circulatory collapse, thrombosis, and embolism. Therefore, the animal should be observed for early signs of fluid depletion with electrolyte imbalance, and corrective measures administered. Excessive loss of potassium in patients receiving digitalis or its glycosides may precipitate digitalis toxicity. Caution should be exercised in animals administered potassium-depleting steroids.

It is important to correct potassium deficiency with dietary supplementation. Caution should be exercised in prescribing enteric-coated potassium tablets.

There have been several reports in human literature, published and unpublished, concerning nonspecific small-bowel lesions consisting of stenosis, with or without ulceration, associated with the administration of enteric-coated thiazides with potassium salts.

These lesions may occur with enteric-coated potassium tablets alone or when they are used with nonenteric-coated thiazides, or certain other oral diuretics. These small-bowel lesions may have caused obstruction, hemorrhage, and perforation. Surgery was frequently required, and deaths have occured. Available information tends to implicate enteric-coated potassium salts, although lesions of this type also occur spontaneously. Therefore, coated potassium-containing formulations should be administered only when indicated and should be discontinued immediately if abdominal pain, distention, nausea, vomiting, or gastro-intestinal bleeding occurs.

Human patients with known sulfonamide sensitivity may show allergic reactions to Salix®; however, these reactions have not been reported in animals.

Sulfonamide diuretics have been reported to decrease arterial responsiveness to pressor amines and to enhance the effect of tubocurarine. Caution should be exercised in administering curare or its derivatives to patients undergoing therapy with Salix® and it is advisable to discontinue Salix® for one day prior to any elective surgery.

DOSAGE AND ADMINISTRATION

The usual dosage of Salix® is 1 to 2 mg/lb. body weight (approximately 2.5 to 5 mg/kg). The lower dosage is suggested for cats.

Administer once or twice daily at 6 to 8 hour intervals either orally, intravenously, or intramuscularly. A prompt diuresis usually ensues from the initial treatment. Diuresis may be initiated by the parenteral administration of Salix® injection and then maintained by oral administration.

The dosage should be adjusted to the individual's response. In severe edematous or refractory cases, the dose may be doubled or increased by increments of 1 mg per pound body weight. The established effective dose should be administered once or twice daily. The daily schedule of administration can be timed to control the period of micturition for the convenience of the client or veterinarian.

Mobilization of the edema may be most efficiently and safely accomplished by utilizing an intermittent daily dosage schedule, i.e. every other day or 2 to 4 consecutive days weekly.

Diuretic therapy should be discontinued after reduction of the edema, or maintained after determining a carefully programmed dosage schedule to prevent recurrence of edema. For long-term treatment, the dose can generally be lowered after the edema has once been reduced. Re-examination and consultations with client will enhance the establishment of a satisfactorily programmed dosage schedule. Clinical examination and serum BUN, CO2 and electrolyte determinations should be performed during the early period of therapy and periodically thereafter, especially in refractory cases. Abnormalities should be corrected or the drug temporarily withdrawn.

DOSAGE: ORAL

DOG AND CAT

One-half to one 50 mg scored tablet per 25 pounds body weight.

One 12.5 mg tablet per 5 to 10 pounds body weight.

Administer once or twice daily, permitting a 6-to 8-hour interval between treatments. In refractory or severe edematous cases, the dosage may be doubled or increase by increments of 1 mg per pound body weight as recommended in preceding paragraphs, "Dosage and Administration".

HOW SUPPLIED

Tablets:

50 mg (scored) tablets

Each tablet contains 50.0 milligrams of furosemide:4-chloro-N-furfuryl-5-sulfamoylanthranilic acid.

12.5 mg tablets

Each tablet contains 12.5 milligrams of furosemide:4-chloro-N-furfuryl-5-sulfamoylanthranilic acid.

STORAGE AND HANDLING

Available in bottles of 500 tablets.

TOXICOLOGY

Acute Toxicity:

The following table illustrates low acute toxicity of Salix® in three different species.

(Two values indicate two different studies.)

LD50 of Salix® in mg/kg body weight
SPECIES | ORAL | INTRAVENOUS
Mouse | 1050-1500 | 308
Rat | 2650-4600 [NOTE: The lower value for the rat oral LD50 was obtained in a group of fasted animals; the higher figure is from a study performed in fed rats. Toxic doses lead to convulsions, ataxia, paralysis and collapse. Animals surviving toxic dosages may become dehydrated and depleted of electrolytes due to the massive diuresis and saluresis.] | 680
Dog | >1000 and >4640 | >300 and >464

Chronic Toxicity:

Chronic Toxicity studies with Salix® were done in a one-year study in rats and dogs. In a one-year study in rats, renal tubular degeneration occured with all doses higher than 50 mg/kg.

A six-month study in dogs revealed calcification and scarring of the renal parenchyma at all doses above 10 mg/kg.

CLINICAL STUDIES

Reproductive Studies:

Reproductive Studies were conducted in mice, rats and rabbits. Only in rabbits administered high doses (equivalent to 10 to 25 times the recommended average dose of 2 mg/kg for dogs and cats) of furosemide during the second trimester period did unexplained maternal deaths and abortions occur. The administration of Salix® is not recommended during the second trimester of pregnancy.

REFERENCES available upon request

Salix® Tablets 12.5 mg and 50 mg

Furosemide (active ingred.) made in Germany. Formulated in Austria.

© 2024, Intervet Inc. (d/b/a Merck Animal Health) Rahway, NJ 07065

Rev. 08/24

220840 R2

PRINCIPAL DISPLAY PANEL - 50 mg Tablet Bottle Label

Salix®
(furosemide tablets)

50mg

Caution: Federal law restricts this
drug to use by or on the order
of a licensed veterinarian.

Do not use if bottle
closure seal is broken.

Store at or below
25° C (77°F)

Keep this and all
medication out of the
reach of children.

500 Tablets

MERCK
Animal Health

PRINCIPAL DISPLAY PANEL - 12.5 mg Tablet Bottle Label

Salix®
(furosemide tablets)

12.5 mg

Caution: Federal law restricts this
drug to use by or on the order of
a licensed veterinarian.

Do not use if bottle closure
seal is broken.

Store at or below 25° C (77°F)

Keep this and all
medication out of the
reach of children.

500 Tablets

MERCK
Animal Health